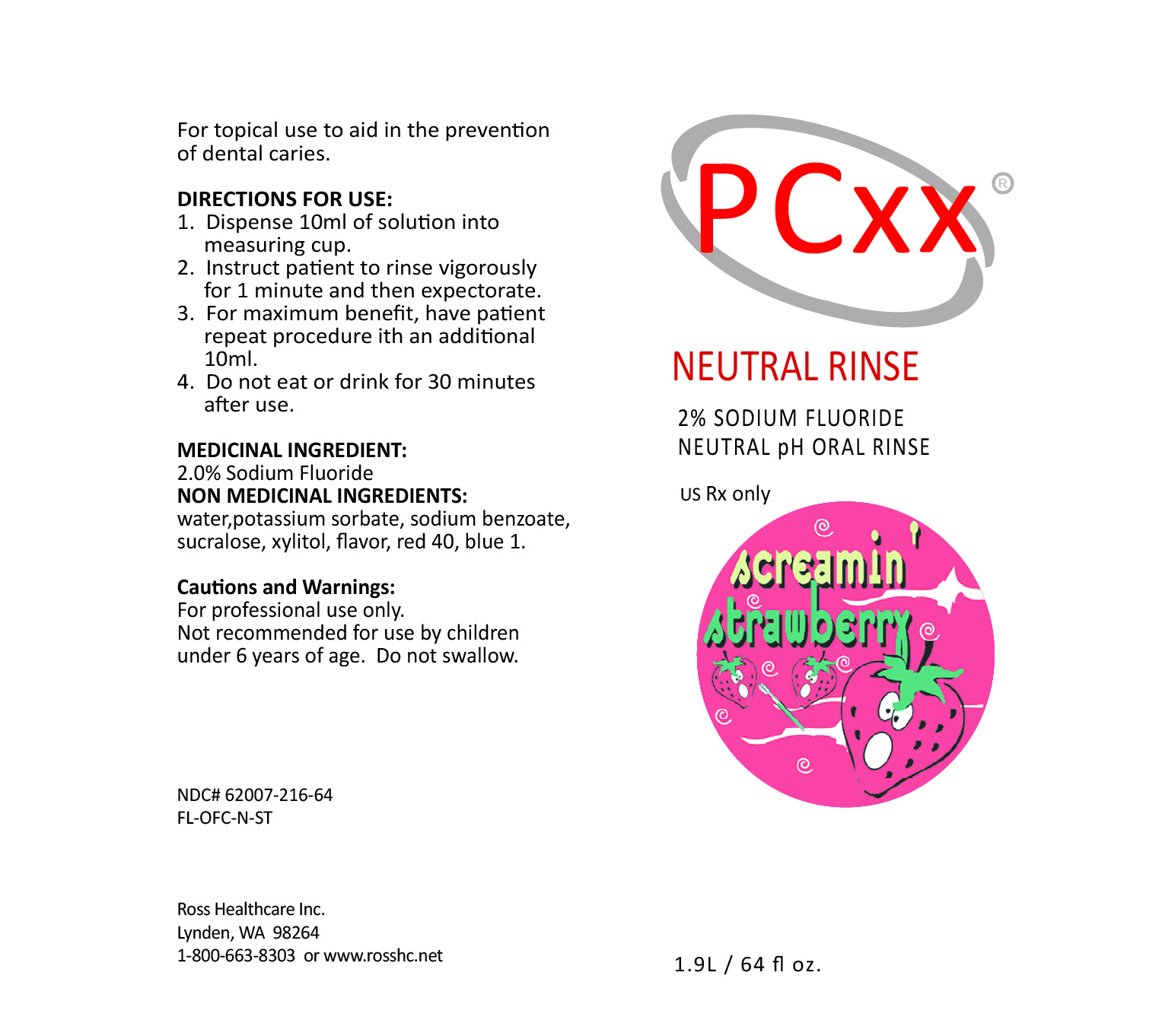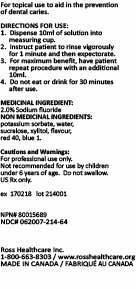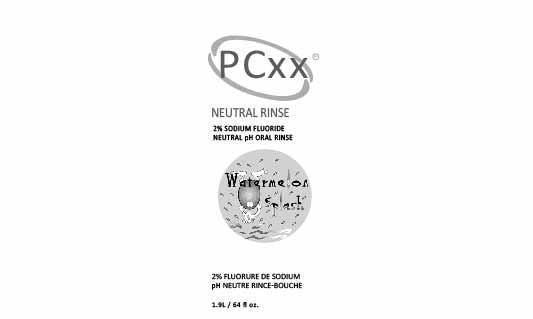 DRUG LABEL: PCXX NEUTRAL RNS STRAWBERRY
NDC: 62007-216 | Form: RINSE
Manufacturer: Ross Healthcare Inc.
Category: prescription | Type: HUMAN PRESCRIPTION DRUG LABEL
Date: 20250904

ACTIVE INGREDIENTS: SODIUM FLUORIDE 2 mg/1 g

PCXX NEUTRAL RNS STRAWBERRY